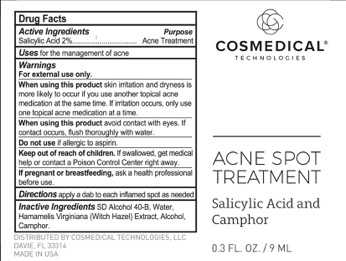 DRUG LABEL: Acne Spot Treatment
NDC: 70060-1505 | Form: LIQUID
Manufacturer: CosMedical Technologies
Category: otc | Type: HUMAN OTC DRUG LABEL
Date: 20251113

ACTIVE INGREDIENTS: SALICYLIC ACID 20 mg/1 mL
INACTIVE INGREDIENTS: WATER; ALCOHOL; WITCH HAZEL

Acne Spot Treatment

PURPOSE

Acne treatment

WARNINGS

For external use only

Keep out of reach of children.

INACTIVE INGREDIENT

SD Alcohol 40-B, Water, Hamamelis Virginiana (Witch Hazel) Extract, Alcohol, Camphor

ACTIVE INGREDIENT

Salicylic Acid 2.0%

INDICATIONS AND USAGE

Acne Treatment

DOSAGE AND ADMINISTRATION

Topical